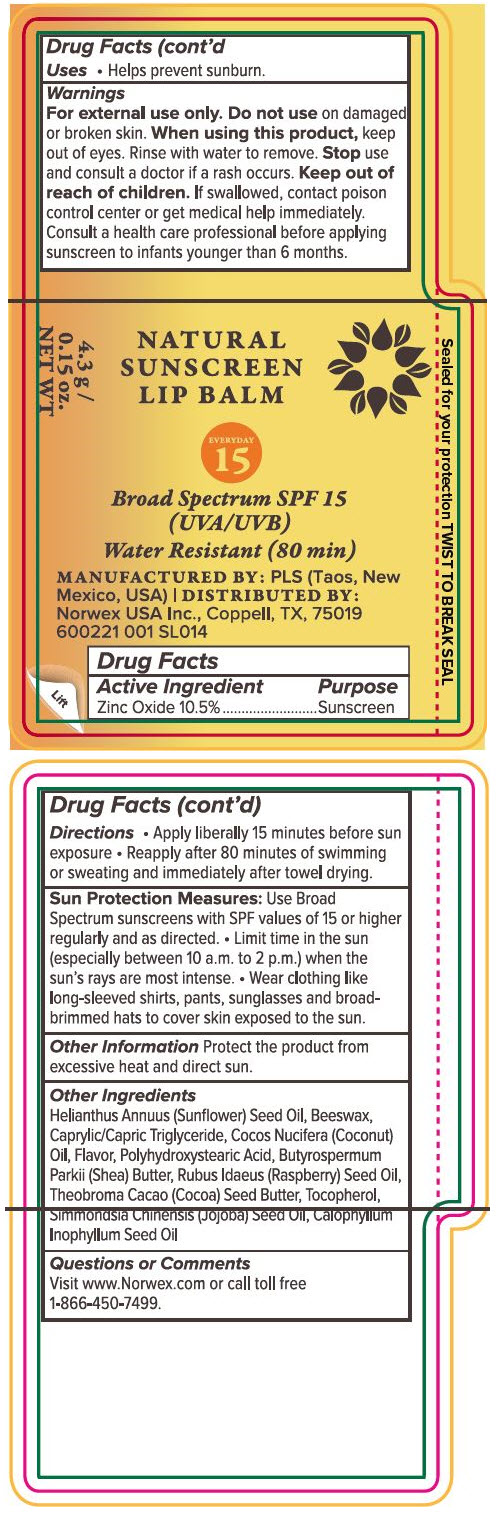 DRUG LABEL: Norwex Natural Sunscreen Lip Balm Broad Spectrum SPF 15
NDC: 66163-1001 | Form: STICK
Manufacturer: Cosmetic Solutions LLC
Category: otc | Type: HUMAN OTC DRUG LABEL
Date: 20230118

ACTIVE INGREDIENTS: Zinc Oxide 10.5 g/100 g
INACTIVE INGREDIENTS: COCOA BUTTER; JOJOBA OIL; TOCOPHEROL; COCONUT OIL; MEDIUM-CHAIN TRIGLYCERIDES; SHEA BUTTER; YELLOW WAX; SUNFLOWER OIL; TAMANU OIL; RASPBERRY SEED OIL; POLYHYDROXYSTEARIC ACID (2300 MW)

Norwex Natural Sunscreen Lip Balm Broad Spectrum SPF 15

Drug Facts

Active Ingredient

Zinc Oxide 10.5%

Purpose

Sunscreen

Uses

- Helps prevent sunburn.

Warnings

For external use only. Do not use on damaged or broken skin. When using this product, keep out of eyes. Rinse with water to remove. Stop use and consult a doctor if a rash occurs.

Keep out of reach of children. If swallowed, contact poison control center or get medical help immediately. Consult a health care professional before applying sunscreen to infants younger than 6 months.

Directions

- Apply liberally 15 minutes before sun exposure
- Reapply after 80 minutes of swimming or sweating and immediately after towel drying.

Sun Protection Measures: Use Broad Spectrum sunscreens with SPF values of 15 or higher regularly and as directed.

- Limit time in the sun (especially between 10 a.m. to 2 p.m.) when the sun's rays are most intense.
- Wear clothing like long-sleeved shirts, pants, sunglasses and broad-brimmed hats to cover skin exposed to the sun.

Other Information

Protect the product from excessive heat and direct sun.

Other Ingredients

Helianthus Annuus (Sunflower) Seed Oil, Beeswax, Caprylic/Capric Triglyceride, Cocos Nucifera (Coconut) Oil, Flavor, Polyhydroxystearic Acid, Butyrospermum Parkii (Shea) Butter, Rubus Idaeus (Raspberry) Seed Oil, Theobroma Cacao (Cocoa) Seed Butter, Tocopherol, Simmondsia Chinensis (Jojoba) Seed Oil, Calophyllum Inophyllum Seed Oil

Questions or Comments

Visit www.Norwex.com or call toll free 1-866-450-7499.

MANUFACTURED BY: PLS (Taos, New Mexico, USA) | DISTRIBUTED BY: Norwex USA Inc., Coppell, TX, 75019

PRINCIPAL DISPLAY PANEL - 4.3 g Cylinder Label

NATURAL
SUNSCREEN
LIP BALM

EVERYDAY
15

Broad Spectrum SPF 15
(UVA/UVB)
Water Resistant (80 min)

Sealed for your protection

4.3 g /
0.15 oz.
NET WT